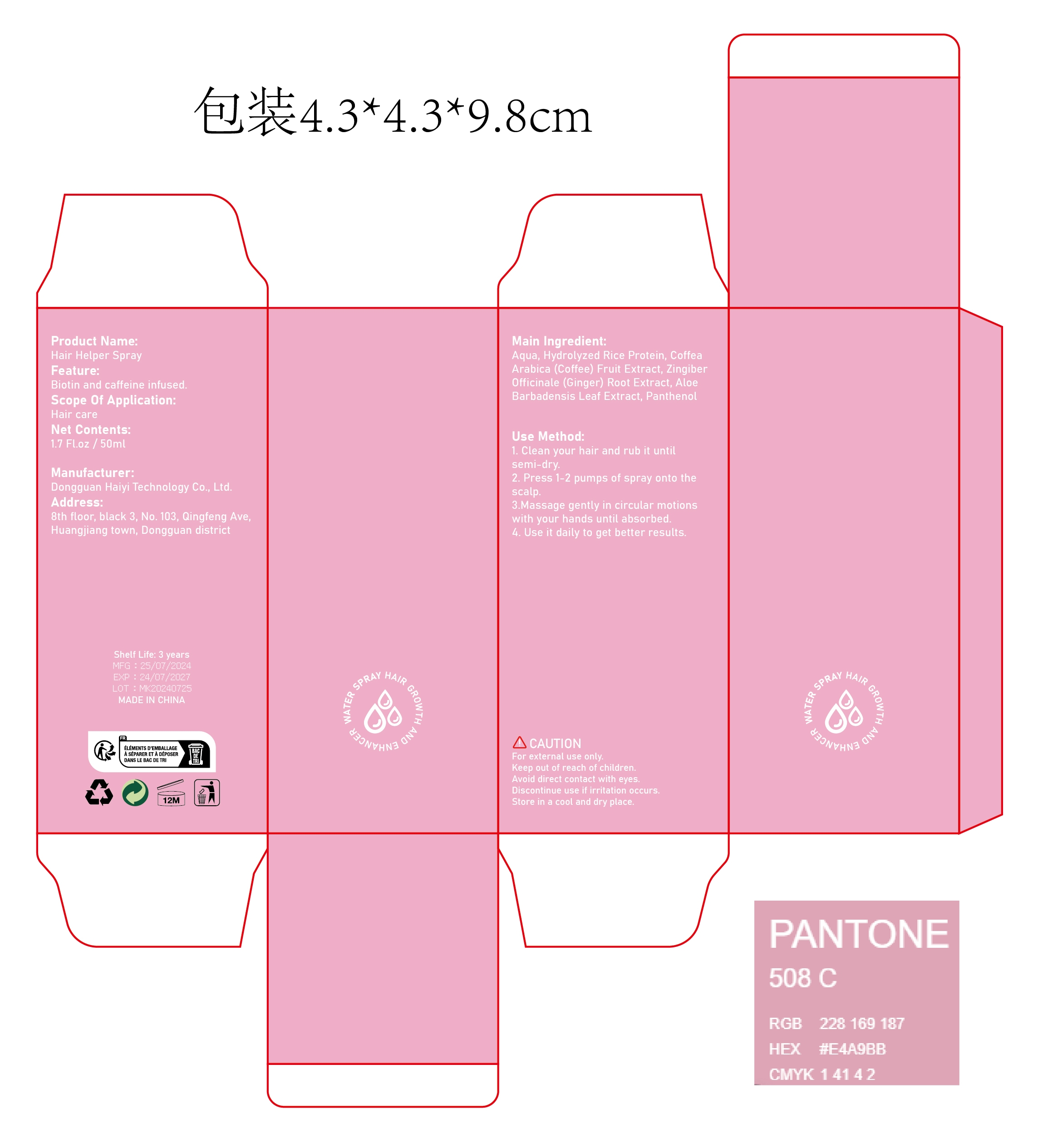 DRUG LABEL: Hair Helper spary
NDC: 84732-027 | Form: SPRAY
Manufacturer: Dongguan Haiyi Technology Co.,Ltd.
Category: otc | Type: HUMAN OTC DRUG LABEL
Date: 20240929

ACTIVE INGREDIENTS: HYDROLYZED RICE PROTEIN (ENZYMATIC; 2000 MW) 1 mg/50 mL
INACTIVE INGREDIENTS: COFFEA ARABICA FRUIT; ALOE VERA LEAF; PANTHENOL; WATER; GINGER

Active ingredient

Hydrolyzed Rice Protein

Inactive ingredient

Coffea Arabica (Coffee) Fruit Extract

Zingiber Officinale (Ginger) Root Extract

Aloe Barbadensis Leaf Extract

Panthenol

Aqua

Purpose section

Infused with Biotin and Caffeine for Hair Growth

Warning

For external use only.

Keep out of reach of children.Avoid direct contact with eyes.

Discontinue use if irritation occurs Store in a cool and dry place.

stop use

This product may cause allergic reactions in asmall number of people.
lf you experience any discomfort,please stop using it immediately.

not use

Not suitable for use by children, pregnantor breast feeding people.

OUT OF CHILDREN

KEEP THE PRODUCT OUT OF REACH OF CHILDREN to

HOW TO USE

1. Clean your hair and rub it untilsemi-dry.

2. Press 1-2 pumps of spray onto thescalp.

3.Massage gently in circular motionswith your hands until absorbed.

4. Use it daily to get better results.

Dosage

take an appropriateamount,Use 2-3 times a week